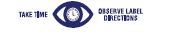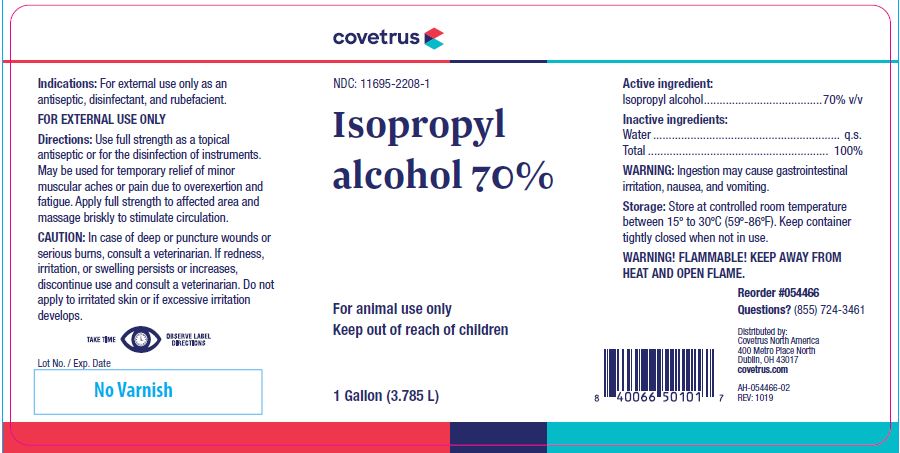 DRUG LABEL: Isopropyl Alcohol
NDC: 11695-2208 | Form: LIQUID
Manufacturer: Covetrus North America
Category: animal | Type: OTC ANIMAL DRUG LABEL
Date: 20241029

ACTIVE INGREDIENTS: ISOPROPYL ALCOHOL 557.25 g/1 L

Isopropyl
alcohol 70%

KEEP OUT OF REACH OF CHILDREN

For animal use only
Keep out of reach of children

HOW SUPPLIED

1 Gallon (3.785 L)

Indications:

For external use only as an antiseptic, disinfectant, and rubefacient.

FOR EXTERNAL USE ONLY

Directions:

Use full strength as a topical antiseptic or for the disinfection of instruments.
May be used for temporary relief of minor muscular aches or pain due to overexertion and fatigue. Apply full strength to affected area and massage briskly to stimulate circulation.

CAUTION:

In case of deep or puncture wounds or serious burns, consult a veterinarian. If redness, irritation, or swelling persists or increases, discontinue use and consult a veterinarian. Do not apply to irritated skin or if excessive irritation develops.

Active ingredient:

Isopropyl alcohol......................................70% v/v

Inactive ingredients:

Water ............................................................ q.s.
Total .......................................................... 100%

WARNING:

Ingestion may cause gastrointestinal irritation, nausea, and vomiting.

Storage:

Store at controlled room temperature between 15º to 30ºC (59º-86ºF). Keep container tightly closed when not in use.

WARNING! FLAMMABLE! KEEP AWAY FROM HEAT AND OPEN FLAME.

INFORMATION FOR OWNERS/CAREGIVERS

Reorder #054466
Questions? (855) 724-3461
Distributed by:
Covetrus North America
400 Metro Place North
Dublin, OH 43017
covetrus.com

AH-054466-02
REV: 1019